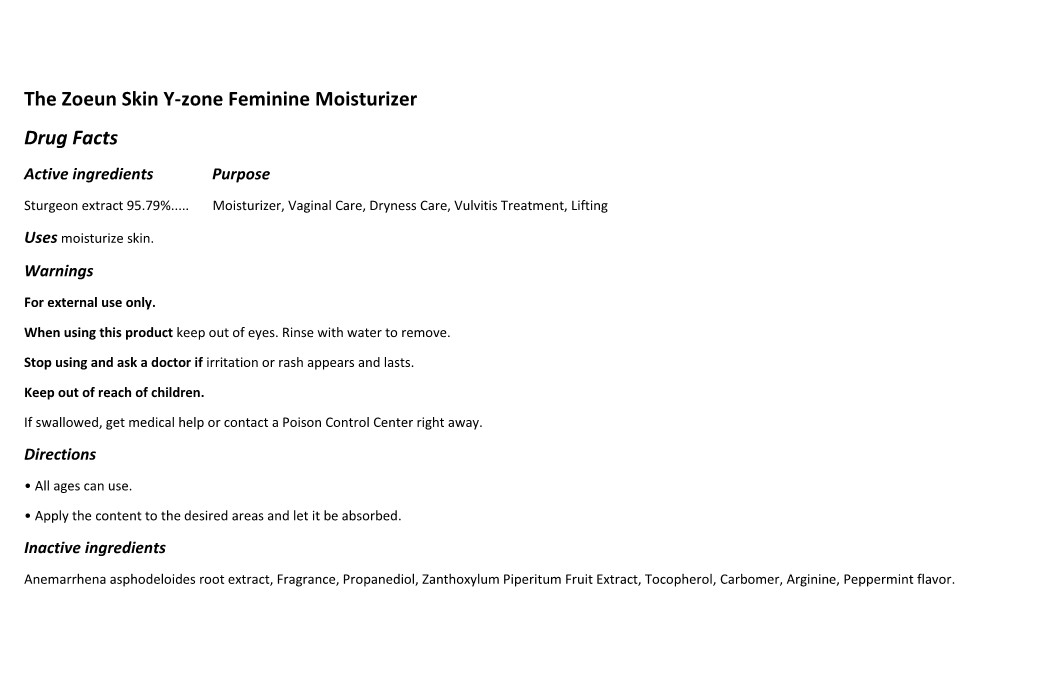 DRUG LABEL: The Zoeun Skin Y-zone Feminine Moisturizer
NDC: 83636-605 | Form: CREAM
Manufacturer: Sturgeonbio Co.,Ltd.
Category: otc | Type: HUMAN OTC DRUG LABEL
Date: 20250120

ACTIVE INGREDIENTS: STURGEON, UNSPECIFIED 95.79 g/100 mL
INACTIVE INGREDIENTS: ARGININE; ANEMARRHENA ASPHODELOIDES ROOT; FRAGRANCE 13576; PEPPERMINT; ZANTHOXYLUM PIPERITUM FRUIT PULP; TOCOPHEROL; PROPANEDIOL; CARBOMER HOMOPOLYMER, UNSPECIFIED TYPE

83636-605 The Zoeun Skin Y-zone Feminine Moisturizer

Active Ingredients

Sturgeon extract 95.79%

Purposes

Moisturizing, Vaginal Care, Dryness Care, Vulvitis Treatment

Uses

moisturize skin.

Warnings

For external use only.

Warnings

When using this product keep out of eyes. Rinse with water to remove.

Warnings

Stop using and ask a doctor if irritation or rash appears and lasts.

Warnings

Keep out of reach of children.

If swallowed, get medical help or contact a Poison Control Center right away.

Directions

• All ages can use.

• Whenever wish to, apply directly to the skin, and let the skin absorb without wiping.

Inactive Ingredients

Anemarrhena asphodeloides root extract, Fragrance, Propanediol, Zanthoxylum Piperitum Fruit Extract, Tocopherol, Carbomer, Arginine, Peppermint flavor.